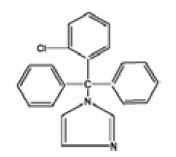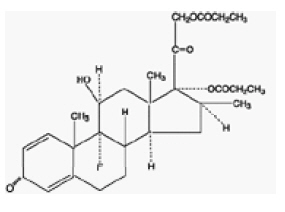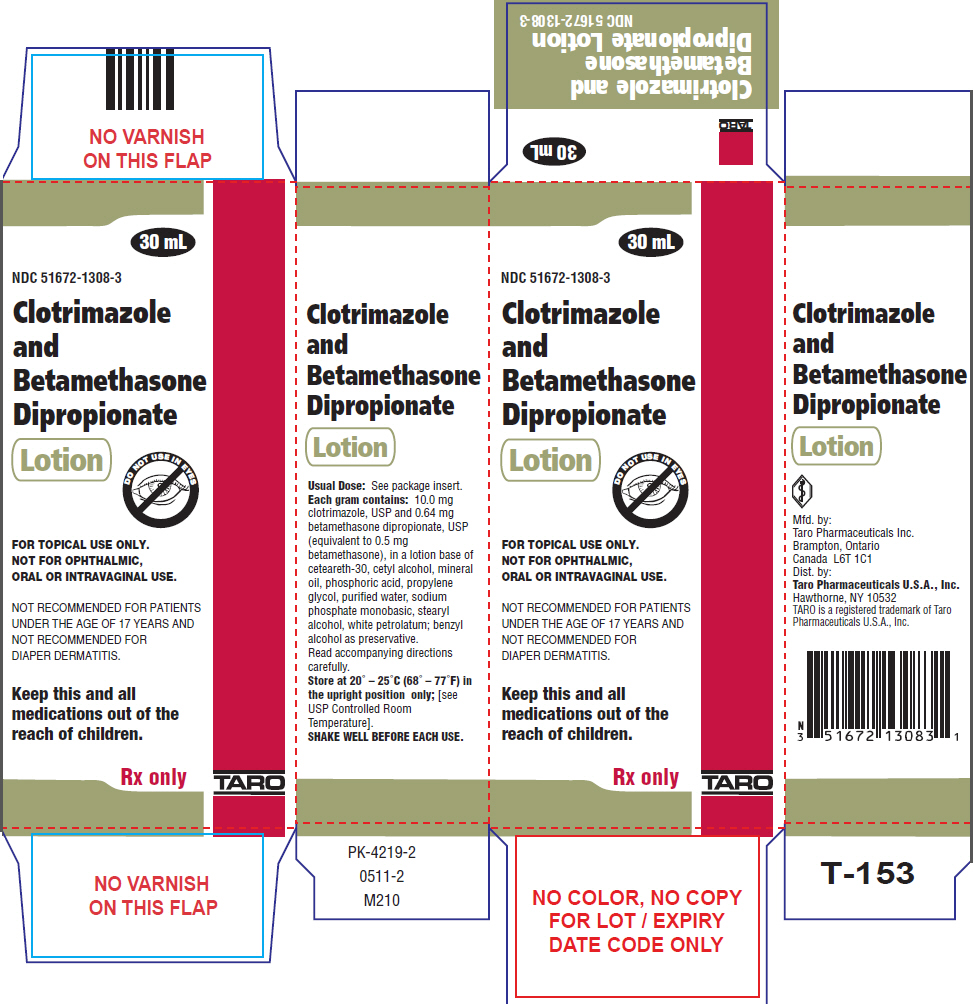 DRUG LABEL: Clotrimazole and Betamethasone Dipropionate
NDC: 51672-1308 | Form: LOTION
Manufacturer: Sun Pharmaceutical Industries, Inc.
Category: prescription | Type: HUMAN PRESCRIPTION DRUG LABEL
Date: 20250707

ACTIVE INGREDIENTS: CLOTRIMAZOLE 10 mg/1 mL; BETAMETHASONE DIPROPIONATE 0.5 mg/1 mL
INACTIVE INGREDIENTS: CETEARETH-30; CETYL ALCOHOL; MINERAL OIL; PHOSPHORIC ACID; PROPYLENE GLYCOL; WATER; SODIUM PHOSPHATE, MONOBASIC, ANHYDROUS; STEARYL ALCOHOL; PETROLATUM; BENZYL ALCOHOL

Clotrimazole and Betamethasone
Dipropionate Lotion

Rx only

FOR TOPICAL USE ONLY. NOT FOR OPHTHALMIC, ORAL, OR INTRAVAGINAL USE. NOT RECOMMENDED FOR PATIENTS UNDER THE AGE OF 17 YEARS AND NOT RECOMMENDED FOR DIAPER DERMATITIS.

DESCRIPTION

Clotrimazole and Betamethasone Dipropionate Lotion contains combinations of clotrimazole, a synthetic antifungal agent, and betamethasone dipropionate, a synthetic corticosteroid, for dermatologic use.

Chemically, clotrimazole is 1-(o-chloro-α,α-diphenylbenzyl) imidazole, with the empirical formula C22H17CIN2, a molecular weight of 344.84, and the following structural formula:

Clotrimazole is an odorless, white crystalline powder, insoluble in water and soluble in ethanol.

Betamethasone dipropionate has the chemical name 9-fluoro-11β,17,21-trihydroxy-16β-methylpregna-1,4-diene-3,20-dione 17,21-dipropionate, with the empirical formula C28H37FO7, a molecular weight of 504.59, and the following structural formula:

Betamethasone dipropionate is a white to creamy white, odorless crystalline powder, insoluble in water.

Each gram of clotrimazole and betamethasone dipropionate lotion contains 10 mg clotrimazole, USP and 0.64 mg betamethasone dipropionate, USP (equivalent to 0.5 mg betamethasone), in a hydrophilic base of ceteareth-30, cetyl alcohol, mineral oil, phosphoric acid, propylene glycol, purified water, sodium phosphate monobasic, stearyl alcohol, white petrolatum; benzyl alcohol as preservative.

Clotrimazole and betamethasone dipropionate lotion is opaque and white in color.

CLINICAL PHARMACOLOGY

Clotrimazole and Betamethasone Dipropionate

No comparative studies have been conducted with clotrimazole and betamethasone dipropionate lotion and clotrimazole alone. Use of corticosteroids in the treatment of a fungal infection may lead to suppression of host inflammation leading to worsening or decreased cure rate.

Clotrimazole

Skin penetration and systemic absorption of clotrimazole following topical application of clotrimazole and betamethasone dipropionate lotion have not been studied. The following information was obtained using 1% clotrimazole solution formulations. Six hours after the application of radioactive clotrimazole 1% solution onto intact and acutely inflamed skin, the concentration of clotrimazole varied from 100 mcg/cm^3in the stratum corneum, to 0.5 to 1 mcg/cm^3in the reticular dermis, and 0.1 mcg/cm^3in the subcutis. No measurable amount of radioactivity (<0.001 mcg/mL) was found in the serum within 48 hours after application under occlusive dressing of 0.5 mL of the solution. Only 0.5% or less of the applied radioactivity was excreted in the urine.

Microbiology

Mechanism of Action

Clotrimazole is an imidazole antifungal agent. Imidazoles inhibit 14-α-demethylation of lanosterol in fungi by binding to one of the cytochrome P-450 enzymes. This leads to the accumulation of 14-α-methylsterols and reduced concentrations of ergosterol, a sterol essential for a normal fungal cytoplasmic membrane. The methylsterols may affect the electron transport system, thereby inhibiting growth of fungi.

Activity In Vivo

Clotrimazole has been shown to be active against most strains of the following dermatophytes, both in vitroand in clinical infections as described in the INDICATIONS AND USAGEsection: Epidermophyton floccosum, Trichophyton mentagrophytes,and Trichophyton rubrum.

Activity In Vitro

In vitro,clotrimazole has been shown to have activity against many dermatophytes, but the clinical significance of this information is unknown.

Drug Resistance

Strains of dermatophytes having a natural resistance to clotrimazole have not been reported. Resistance to azoles including clotrimazole has been reported in some Candidaspecies.

No single-step or multiple-step resistance to clotrimazole has developed during successive passages of Trichophyton mentagrophytes.

Betamethasone Dipropionate

Betamethasone dipropionate, a corticosteroid, has been shown to have topical (dermatologic) and systemic pharmacologic and metabolic effects characteristic of this class of drugs.

Pharmacokinetics

The extent of percutaneous absorption of topical corticosteroids is determined by many factors, including the vehicle, the integrity of the epidermal barrier and the use of occlusive dressings (see DOSAGE AND ADMINISTRATION). Topical corticosteroids can be absorbed from normal intact skin. Inflammation and/or other disease processes in the skin may increase percutaneous absorption of topical corticosteroids. Occlusive dressings substantially increase the percutaneous absorption of topical corticosteroids (see DOSAGE AND ADMINISTRATION).

Once absorbed through the skin, the pharmacokinetics of topical corticosteroids are similar to systemically administered corticosteroids. Corticosteroids are bound to plasma proteins in varying degrees. Corticosteroids are metabolized primarily in the liver and are then excreted by the kidneys. Some of the topical corticosteroids and their metabolites are also excreted into the bile. Studies performed with clotrimazole and betamethasone dipropionate lotion indicate that this topical combination antifungal/corticosteroid may have vasoconstrictor potencies in a range that is comparable to high-potency topical corticosteroids. Therefore, use is not recommended in patients less than 17 years of age, in diaper dermatitis, and under occlusion.

CLINICAL STUDIES (Clotrimazole and Betamethasone Dipropionate Lotion)

In the treatment of tinea pedis twice daily for 4 weeks, clotrimazole and betamethasone dipropionate lotion was shown to be superior to vehicle in relieving symptoms of erythema, scaling, pruritus, and maceration at Week 2. Clotrimazole and betamethasone dipropionate lotion was also shown to have a superior mycological cure rate compared to vehicle 2 weeks after discontinuation of treatment. It is unclear if the relief of symptoms at 2 weeks in this clinical study with clotrimazole and betamethasone dipropionate lotion was due to the contribution of betamethasone dipropionate, clotrimazole, or both.

In the treatment of tinea cruris twice daily for 2 weeks, clotrimazole and betamethasone dipropionate lotion was shown to be superior to vehicle in the relief of symptoms of erythema, scaling, and pruritus after 3 days. It is unclear if the relief of symptoms after 3 days in this clinical study with clotrimazole and betamethasone dipropionate lotion was due to the contribution of betamethasone dipropionate, clotrimazole, or both.

The comparative efficacy and safety of clotrimazole and betamethasone dipropionate lotion versus clotrimazole alone in a lotion vehicle have not been studied in the treatment of tinea pedis or tinea cruris or tinea corporis. The comparative efficacy and safety of clotrimazole and betamethasone dipropionate lotion and clotrimazole and betamethasone dipropionate cream have also not been studied.

INDICATIONS AND USAGE

Clotrimazole and betamethasone dipropionate lotion is indicated in patients 17 years and older for the topical treatment of symptomatic inflammatory tinea pedis, tinea cruris, and tinea corporis due to Epidermophyton floccosum, Trichophyton mentagrophytesand Trichophyton rubrum.Effective treatment without the risks associated with topical corticosteroid use may be obtained using a topical antifungal agent that does not contain a corticosteroid, especially for noninflammatory tinea infections. The efficacy of clotrimazole and betamethasone dipropionate lotion for the treatment of infections caused by zoophilic dermatophytes (e.g., Microsporum canis) has not been established.

CONTRAINDICATIONS

Clotrimazole and betamethasone dipropionate lotion is contraindicated in patients who are sensitive to clotrimazole, betamethasone dipropionate, other corticosteroids or imidazoles, or to any ingredient in this preparation.

PRECAUTIONS

General

Systemic absorption of topical corticosteroids can produce reversible hypothalamic-pituitary-adrenal (HPA) axis suppression with the potential for glucocorticosteroid insufficiency after withdrawal of treatment. Manifestations of Cushing's syndrome, hyperglycemia, and glucosuria can also be produced in some patients by systemic absorption of topical corticosteroids while on treatment.

Conditions which augment systemic absorption include use over large surface areas, prolonged use, and use under occlusive dressings. Use of more than one corticosteroid-containing product at the same time may increase total systemic glucocorticoid exposure. Patients applying clotrimazole and betamethasone dipropionate lotion to a large surface area or to areas under occlusion should be evaluated periodically for evidence of HPA axis suppression. This may be done by using the ACTH stimulation, morning plasma cortisol, and urinary-free cortisol tests.

If HPA axis suppression is noted, an attempt should be made to withdraw the drug, to reduce the frequency of application, or to substitute a less potent corticosteroid. Recovery of HPA axis function is generally prompt upon discontinuation of topical corticosteroids. Infrequently, signs and symptoms of glucocorticosteroid insufficiency may occur, requiring supplemental systemic corticosteroids.

In a small study, clotrimazole and betamethasone dipropionate cream was applied using large dosages, 7 g daily for 14 days (BID) to the crural area of normal adult subjects. Three of the eight normal subjects on whom clotrimazole and betamethasone dipropionate cream was applied exhibited low morning plasma cortisol levels during treatment. One of these subjects had an abnormal Cortrosyn test. The effect on morning plasma cortisol was transient and subjects recovered one week after discontinuing dosing. In addition, two separate studies in pediatric patients demonstrated adrenal suppression as determined by cosyntropin testing (see PRECAUTIONS, Pediatric Use).

Pediatric patients may be more susceptible to systemic toxicity from equivalent doses due to their larger skin surface to body mass ratios (see PRECAUTIONS, Pediatric Use).

If irritation develops, clotrimazole and betamethasone dipropionate lotion should be discontinued and appropriate therapy instituted.

THE SAFETY OF CLOTRIMAZOLE AND BETAMETHASONE DIPROPIONATE LOTION HAS NOT BEEN DEMONSTRATED IN THE TREATMENT OF DIAPER DERMATITIS. ADVERSE EVENTS CONSISTENT WITH CORTICOSTEROID USE HAVE BEEN OBSERVED IN PATIENTS TREATED WITH CLOTRIMAZOLE AND BETAMETHASONE DIPROPIONATE CREAM FOR DIAPER DERMATITIS. THE USE OF CLOTRIMAZOLE AND BETAMETHASONE DIPROPIONATE LOTION IN THE TREATMENT OF DIAPER DERMATITIS IS NOT RECOMMENDED.

Information for Patients

Patients using clotrimazole and betamethasone dipropionate lotion should receive the following information and instructions:

1. The medication is to be used as directed by the physician and is not recommended for use longer than the prescribed time period. It is for external use only. Avoid contact with the eyes, the mouth, or intravaginally.
2. This medication is to be used for the full prescribed treatment time, even though the symptoms may have improved. Notify the physician if there is no improvement after 1 week of treatment for tinea cruris or tinea corporis, or after 2 weeks for tinea pedis.
3. This medication should only be used for the disorder for which it was prescribed.
4. Other corticosteroid-containing products should not be used with clotrimazole and betamethasone dipropionate without first talking with your physician.
5. The treated skin area should not be bandaged, covered, or wrapped so as to be occluded (see DOSAGE AND ADMINISTRATION).
6. Any signs of local adverse reactions should be reported to your physician.
7. Patients should avoid sources of infection or reinfection.
8. When using clotrimazole and betamethasone dipropionate lotion in the groin area, patients should use the medication for 2 weeks only, and apply the lotion sparingly. Patients should wear loose-fitting clothing. Notify the physician if the condition persists after 2 weeks.
9. The safety of clotrimazole and betamethasone dipropionate lotion has not been demonstrated in the treatment of diaper dermatitis. The use of clotrimazole and betamethasone dipropionate lotion in the treatment of diaper dermatitis is not recommended.

Laboratory Tests

If there is a lack of response to clotrimazole and betamethasone dipropionate lotion, appropriate confirmation of the diagnosis, including possible mycological studies, is indicated before instituting another course of therapy.

The following tests may be helpful in evaluating HPA axis suppression due to the corticosteroid components:

- Urinary-free cortisol test
- Morning plasma cortisol test
- ACTH (cosyntropin) stimulation test

Carcinogenesis, Mutagenesis, Impairment of Fertility

There are no adequate laboratory animal studies with either the combination of clotrimazole and betamethasone dipropionate or with either component individually to evaluate carcinogenesis.

Betamethasone was negative in the bacterial mutagenicity assay (Salmonella typhimuriumand Escherichia coli)and in the mammalian cell mutagenicity assay (CHO/HGPRT). It was positive in the in vitrohuman lymphocyte chromosome aberration assay, and equivocal in the in vivomouse bone marrow micronucleus assay. This pattern of response is similar to that of dexamethasone and hydrocortisone.

Reproductive studies with betamethasone dipropionate carried out in rabbits at doses of 1.0 mg/kg by the intramuscular route and in mice up to 33 mg/kg by the intramuscular route indicated no impairment of fertility except for dose-related increases in fetal resorption rates in both species. These doses are approximately 5- and 38-fold the maximum human dose based on body surface areas, respectively.

In a combined study of the effects of clotrimazole on fertility, teratogenicity, and postnatal development, male and female rats were dosed orally (diet admixture) with levels of 5, 10, 25, or 50 mg/kg/day (approximately 1 to 8 times the maximum dose in a 60-kg adult based on body surface area) from 10 weeks prior to mating until 4 weeks postpartum. No adverse effects on the duration of estrous cycle, fertility, or duration of pregnancy were noted.

Pregnancy

Teratogenic Effects

Pregnancy Category C

There have been no teratogenic studies performed in animals or humans with the combination of clotrimazole and betamethasone dipropionate. Corticosteroids are generally teratogenic in laboratory animals when administered at relatively low dosage levels.

Studies in pregnant rats with intravaginal doses up to 100 mg/kg (15 times the maximum human dose) revealed no evidence of fetotoxicity due to clotrimazole exposure.

No increase in fetal malformations was noted in pregnant rats receiving oral (gastric tube) clotrimazole doses up to 100 mg/kg/day during gestation Days 6 to 15. However, clotrimazole dosed at 100 mg/kg/day was embryotoxic (increased resorptions), fetotoxic (reduced fetal weights), and maternally toxic (reduced body weight gain) to rats. Clotrimazole dosed at 200 mg/kg/day (30 times the maximum human dose) was maternally lethal, and therefore fetuses were not evaluated in this group. Also in this study, doses up to 50 mg/kg/day (8 times the maximum human dose) had no adverse effects on dams or fetuses. However, in the combined fertility, teratogenicity, and postnatal development study described above, 50 mg/kg clotrimazole, was associated with reduced maternal weight gain and reduced numbers of offspring reared to 4 weeks.

Oral clotrimazole doses of 25, 50, 100, and 200 mg/kg/day (2 to 15 times the maximum human dose) were not teratogenic in mice. No evidence of maternal toxicity or embryotoxicity was seen in pregnant rabbits dosed orally with 60, 120, or 180 mg/kg/day (18 to 55 times the maximum human dose).

Betamethasone dipropionate has been shown to be teratogenic in rabbits when given by the intramuscular route at doses of 0.05 mg/kg. This dose is approximately one-fifth the maximum human dose. The abnormalities observed included umbilical hernias, cephalocele and cleft palates.

Betamethasone dipropionate has not been tested for teratogenic potential by the dermal route of administration. Some corticosteroids have been shown to be teratogenic after dermal application to laboratory animals.

There are no adequate and well-controlled studies in pregnant women of the teratogenic effects of topically applied corticosteroids. Therefore, clotrimazole and betamethasone dipropionate lotion should be used during pregnancy only if the potential benefit justifies the potential risk to the fetus.

Nursing Mothers

Systemically administered corticosteroids appear in human milk and could suppress growth, interfere with endogenous corticosteroid production, or cause other untoward effects. It is not known whether topical administration of corticosteroids could result in sufficient systemic absorption to produce detectable quantities in human milk. Because many drugs are excreted in human milk, caution should be exercised when clotrimazole and betamethasone dipropionate lotion is administered to a nursing woman.

Pediatric Use

Adverse events consistent with corticosteroid use have been observed in patients under 12 years of age treated with clotrimazole and betamethasone dipropionate cream. In open-label studies, 17 of 43 (39.5%) evaluable pediatric patients (aged 12 to 16 years old) using clotrimazole and betamethasone dipropionate cream for treatment of tinea pedis demonstrated adrenal suppression as determined by cosyntropin testing. In another open-label study, 8 of 17 (47.1%) evaluable pediatric patients (aged 12 to 16 years old) using clotrimazole and betamethasone dipropionate cream for treatment of tinea cruris demonstrated adrenal suppression as determined by cosyntropin testing. THE USE OF CLOTRIMAZOLE AND BETAMETHASONE DIPROPIONATE LOTION IN THE TREATMENT OF PATIENTS UNDER 17 YEARS OF AGE OR PATIENTS WITH DIAPER DERMATITIS IS NOT RECOMMENDED.

Because of higher ratio of skin surface area to body mass, pediatric patients under the age of 12 years are at a higher risk with clotrimazole and betamethasone dipropionate lotion. The studies described above suggest that pediatric patients under the age of 17 years may also have this risk. They are at increased risk of developing Cushing's syndrome while on treatment and adrenal insufficiency after withdrawal of treatment. Adverse effects, including striae and growth retardation, have been reported with inappropriate use of clotrimazole and betamethasone dipropionate cream in infants and children (see PRECAUTIONSand ADVERSE REACTIONS).

Hypothalamic-pituitary-adrenal (HPA) axis suppression, Cushing's syndrome, linear growth retardation, delayed weight gain, and intracranial hypertension have been reported in children receiving topical corticosteroids. Manifestations of adrenal suppression in children include low plasma cortisol levels and absence of response to ACTH stimulation. Manifestations of intracranial hypertension include bulging fontanelles, headaches, and bilateral papilledema.

Geriatric Use

Clinical studies of clotrimazole and betamethasone dipropionate lotion did not include sufficient numbers of subjects aged 65 and over to determine whether they respond differently from younger subjects. Postmarket adverse event reporting for clotrimazole and betamethasone dipropionate cream in patients aged 65 and above includes reports of skin atrophy and rare reports of skin ulceration. Caution should be exercised with the use of these corticosteroid-containing topical products on thinning skin. THE USE OF CLOTRIMAZOLE AND BETAMETHASONE DIPROPIONATE LOTION UNDER OCCLUSION, SUCH AS IN DIAPER DERMATITIS, IS NOT RECOMMENDED.

ADVERSE REACTIONS

Adverse reactions reported for clotrimazole and betamethasone dipropionate lotion in clinical trials were burning and dry skin in 1.6% of patients and stinging in less than 1% of patients.

The following local adverse reactions have been reported with topical corticosteroids and may occur more frequently with the use of occlusive dressings. These reactions are listed in an approximate decreasing order of occurrence: itching, irritation, dryness, folliculitis, hypertrichosis, acneiform eruptions, hypopigmentation, perioral dermatitis, allergic contact dermatitis, maceration of the skin, secondary infection, skin atrophy, striae, miliaria, capillary fragility (ecchymoses), telangiectasia, and sensitization (local reactions upon repeated application of product).

Systemic absorption of topical corticosteroids has produced reversible hypothalamic-pituitary-adrenal (HPA) axis suppression, manifestations of Cushing's syndrome, hyperglycemia, and glucosuria in some patients.

Adverse reactions reported with the use of clotrimazole are as follows: erythema, stinging, blistering, peeling, edema, pruritus, urticaria, and general irritation of the skin.

OVERDOSAGE

Amounts greater than 45 mL/week of clotrimazole and betamethasone dipropionate lotion should not be used. Acute overdosage with topical application of clotrimazole and betamethasone dipropionate lotion is unlikely and would not be expected to lead to a life-threatening situation. Clotrimazole and betamethasone dipropionate lotion should not be used for longer than the prescribed time period.

Topically applied corticosteroids, such as the one contained in clotrimazole and betamethasone dipropionate lotion can be absorbed in sufficient amounts to produce systemic effects (see PRECAUTIONS).

DOSAGE AND ADMINISTRATION

Gently massage sufficient clotrimazole and betamethasone dipropionate lotion into the affected skin areas twice a day, in the morning and evening.

Clotrimazole and betamethasone dipropionate lotion should notbe used longer than 2 weeks in the treatment of tinea corporis or tinea cruris, and amounts greater than 45 mL per week of clotrimazole and betamethasone dipropionate lotion should not be used. If a patient with tinea corporis or tinea cruris shows no clinical improvement after one week of treatment with clotrimazole and betamethasone dipropionate lotion, the diagnosis should be reviewed.

Clotrimazole and betamethasone dipropionate lotion should notbe used longer than 4 weeks in the treatment of tinea pedis and amounts greater than 45 mL per week of clotrimazole and betamethasone dipropionate lotion should not be used. If a patient with tinea pedis shows no clinical improvement after 2 weeks of treatment with clotrimazole and betamethasone dipropionate lotion, the diagnosis should be reviewed.

Clotrimazole and betamethasone dipropionate lotion should not be used with occlusive dressings.

HOW SUPPLIED

Clotrimazole and Betamethasone Dipropionate Lotion is supplied in 30-mL bottles (NDC 51672-1308-3); box of one.

STORAGE AND HANDLING

Store at 20° to 25°C (68° to 77°F) in the upright position only;[see USP Controlled Room Temperature].

SHAKE WELL BEFORE EACH USE.

Mfd by:
Taro Pharmaceuticals Inc., Brampton, Ontario, Canada L6T 1C1

Dist. by:
Taro Pharmaceuticals U.S.A., Inc., Hawthorne, NY 10532

Revised: May, 2016
PK-2584-4 206

Patient Information Leaflet

Patient's Instructions for Use

Clotrimazole and Betamethasone Dipropionate Lotion

SHAKE LOTION WELL BEFORE EACH USE

Rx only

What is clotrimazole and betamethasone dipropionate lotion?

Clotrimazole and betamethasone dipropionate lotion is a medication used on the skin to treat fungal infections of the feet, groin, and body, as diagnosed by your doctor. Clotrimazole and betamethasone dipropionate lotion should be used for fungal infections that are inflamed and have symptoms of redness and/or itching. Talk to your doctor if your fungal infection does not have these symptoms. Clotrimazole and betamethasone dipropionate lotion contains a corticosteroid. Notify your doctor if you notice side effects with the use of clotrimazole betamethasone dipropionate lotion (see "What are the possible side effects of clotrimazole and betamethasone dipropionate lotion?"below). Clotrimazole and betamethasone dipropionate lotion is not to be used in the eyes, in the mouth, or in the vagina.

How does clotrimazole and betamethasone dipropionate lotion work?

Clotrimazole and betamethasone dipropionate lotion is a combination of an antifungal agent (clotrimazole) and a corticosteroid (betamethasone dipropionate). Clotrimazole works against fungus. Betamethasone dipropionate, a corticosteroid, is used to help relieve redness, swelling, itching, and other discomforts of fungal infections.

Who should NOT use clotrimazole and betamethasone dipropionate lotion?

Clotrimazole and betamethasone dipropionate lotion is not recommended for use in patients under the age of 17 years. Clotrimazole and betamethasone dipropionate lotion is not recommended for use in diaper rash.

Patients who are sensitive to clotrimazole and betamethasone dipropionate, other corticosteroids or imidazoles, or any ingredients in the preparation should not use clotrimazole and betamethasone dipropionate lotion.

How should I use clotrimazole and betamethasone dipropionate lotion?

Gently massage sufficient clotrimazole and betamethasone dipropionate lotion into the affected and surrounding skin areas twice a day, in the morning and evening. Treatment for 2 weeks on the groin or on the body, and for 4 weeks on the feet is recommended. The use of clotrimazole and betamethasone dipropionate lotion for longer than 4 weeks is not recommended for any condition. Prolonged use of clotrimazole and betamethasone dipropionate lotion may lead to unwanted side effects.

What other important information should I know about clotrimazole and betamethasone dipropionate lotion?

- This medication is to be used for the full prescribed treatment time, even though the symptoms may have improved. Notify your doctor if there is no improvement after 1 week of treatment on the groin or body or after 2 weeks on the feet.
- This medication should only be used for the disorder for which it was prescribed.
- The treated skin area should not be bandaged or otherwise covered or wrapped.
- Other corticosteroid-containing products should not be used with clotrimazole and betamethasone dipropionate lotion without first talking with your physician.
- Any signs of side effects where clotrimazole and betamethasone dipropionate lotion is applied should be reported to your doctor.
- When using clotrimazole and betamethasone dipropionate lotion in the groin area, it is especially important to use the medication for 2 weeks only, and to apply the lotion sparingly. You should tell your doctor if your problem persists after 2 weeks. You should also wear loose-fitting clothing so as to avoid tightly covering the area where clotrimazole and betamethasone dipropionate lotion is applied.
- This medication is not recommended for use in diaper rash.

What are the possible side effects of clotrimazole and betamethasone dipropionate lotion?

The following side effects have been reported with topical corticosteroid medications: itching, irritation, dryness, infection of the hair follicles, increased hair, acne, fragile blood vessels, spider veins, sensitization (local reactions upon repeated application of product), change in skin color, allergic skin reaction, skin thinning, and stretch marks. Hormone imbalance (adrenal suppression) was demonstrated in clinical studies in children.

Can clotrimazole and betamethasone dipropionate lotion be used if I am pregnant or plan to become pregnant or if I am nursing?

Before using clotrimazole and betamethasone dipropionate lotion, tell your doctor if you are pregnant or plan to become pregnant. Also, tell your doctor if you are nursing.

How should clotrimazole and betamethasone dipropionate lotion be stored?

Clotrimazole and betamethasone dipropionate lotion should be stored at 20˚ to 25˚C (68˚ to 77˚F) in the upright position only; [see USP Controlled Room Temperature]. Shake well before using clotrimazole and betamethasone dipropionate lotion.

General advice about prescription medicines

This medicine was prescribed for your particular condition. Only use clotrimazole and betamethasone dipropionate lotion to treat the condition for which your doctor has prescribed. Do not give clotrimazole and betamethasone dipropionate lotion to other people. It may harm them.

This leaflet summarizes the most important information about clotrimazole and betamethasone dipropionate lotion. If you would like more information, talk with your doctor. You can ask your pharmacist or doctor for information about clotrimazole and betamethasone dipropionate lotion that is written for health professionals.

Mfd by:Taro Pharmaceuticals Inc. Brampton, Ontario, Canada L6T 1C1

Dist. by: Taro Pharmaceuticals U.S.A., Inc.Hawthorne, NY 10532

Revised: May, 2016
PK-2584-4 206

PRINCIPAL DISPLAY PANEL - 30 mL Bottle Carton

30 mL

NDC 51672-1308-3

Clotrimazole
and
Betamethasone
Dipropionate
Lotion

DO NOT USE IN EYES

FOR TOPICAL USE ONLY.
NOT FOR OPHTHALMIC,
ORAL OR INTRAVAGINAL USE.

NOT RECOMMENDED FOR PATIENTS
UNDER THE AGE OF 17 YEARS AND
NOT RECOMMENDED FOR
DIAPER DERMATITIS.

Keep this and all
medications out of the
reach of children.

Rx only

TARO